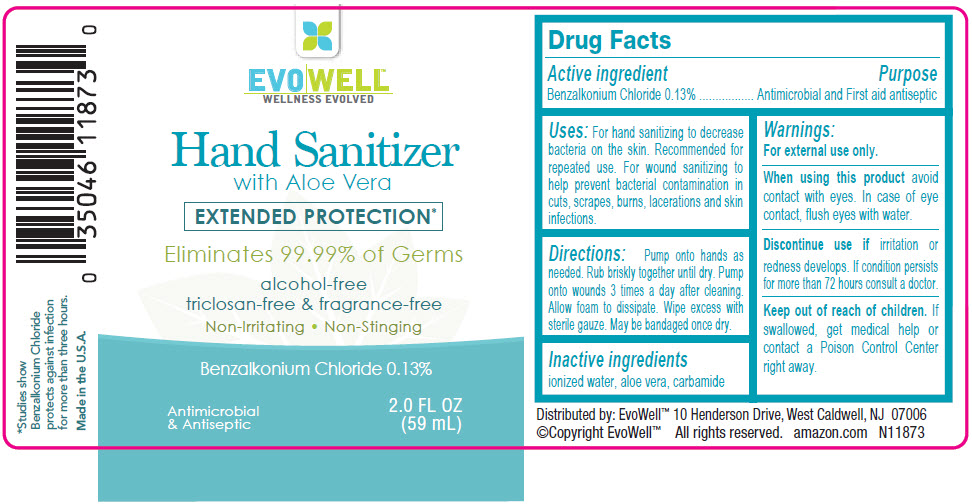 DRUG LABEL: Evowell Hand Sanitizer with Aloe Vera
NDC: 74154-005 | Form: LIQUID
Manufacturer: Windmill Health Products, LLC
Category: otc | Type: HUMAN OTC DRUG LABEL
Date: 20220204

ACTIVE INGREDIENTS: Benzalkonium Chloride 130 mg/100 mL
INACTIVE INGREDIENTS: water; aloe vera leaf; urea

Evowell™ Hand Sanitizer with Aloe Vera

Drug Facts

Active ingredient

Benzalkonium Chloride 0.13%

Purpose

Antimicrobial and First aid antiseptic

Uses

For hand sanitizing to decrease bacteria on the skin. Recommended for repeated use. For wound sanitizing to help prevent bacterial contamination in cuts, scrapes, burns, lacerations and skin infections.

Directions

Pump onto hands as needed. Rub briskly together until dry. Pump onto wounds 3 times a day after cleaning. Allow foam to dissipate. Wipe excess with sterile gauze. May be bandaged once dry.

Inactive ingredients

ionized water, aloe vera, carbamide

Warnings

For external use only.

When using this product avoid contact with eyes. In case of eye contact, flush eyes with water.

STOP USE

Discontinue use if irritation or redness develops. If condition persists for more than 72 hours consult a doctor.

Keep out of reach of children. If swallowed, get medical help or contact a Poison Control Center right away.

Distributed by: EvoWell™ 10 Henderson Drive, West Caldwell, NJ 07006

PRINCIPAL DISPLAY PANEL - 59 mL Bottle Label

EVOWELL™
WELLNESS EVOLVED

Hand Sanitizer
with Aloe Vera

EXTENDED PROTECTION*

Eliminates 99.99% of Germs

alcohol-free
triclosan-free & fragrance-free

Non-Irritating • Non-Stinging

Benzalkonium Chloride 0.13%

Antimicrobial
& Antiseptic

2.0 FL OZ
(59 mL)